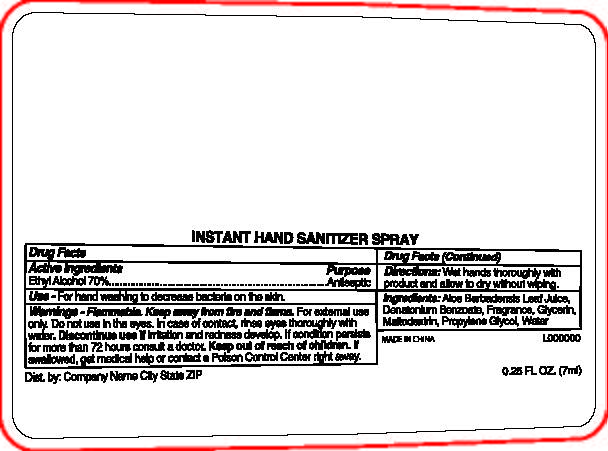 DRUG LABEL: Instant Hand Sanitizer
NDC: 65692-2083 | Form: LIQUID
Manufacturer: Raining Rose, Inc.
Category: otc | Type: HUMAN OTC DRUG LABEL
Date: 20241107

ACTIVE INGREDIENTS: ALCOHOL 70 mL/100 mL
INACTIVE INGREDIENTS: MALTODEXTRIN; WATER; DENATONIUM BENZOATE; PROPYLENE GLYCOL; ALOE VERA LEAF; GLYCERIN

Active Ingredient

Ethyl Alcohol 70%

Purpose

Antiseptic

Indications and Usage

For hand washing to decrease bacteria on the skin.

Warnings

Warnings• For external use only
• Flammable, keep away from fire or flame
• Do not use in eyes. In case of contact, rinse eyes thorougly with water.

• Discontinue use if irritation and redness develop.If condition persists for more than 72 hours consult a doctor.

Keep Out of Reach of Children. If swallowed, get medical help or contact a Poison Control Center right away.

Dosage and Admistration

Wet hands thoroughly with product and allow to dry without wiping.

Inactive Ingredients

Inactive Ingredients: Aloe Barbadensis Leaf Juice, Denatonium Benzoate, Fragrance, Glycerin, Maltodextrin, Propylene Glycol, Water